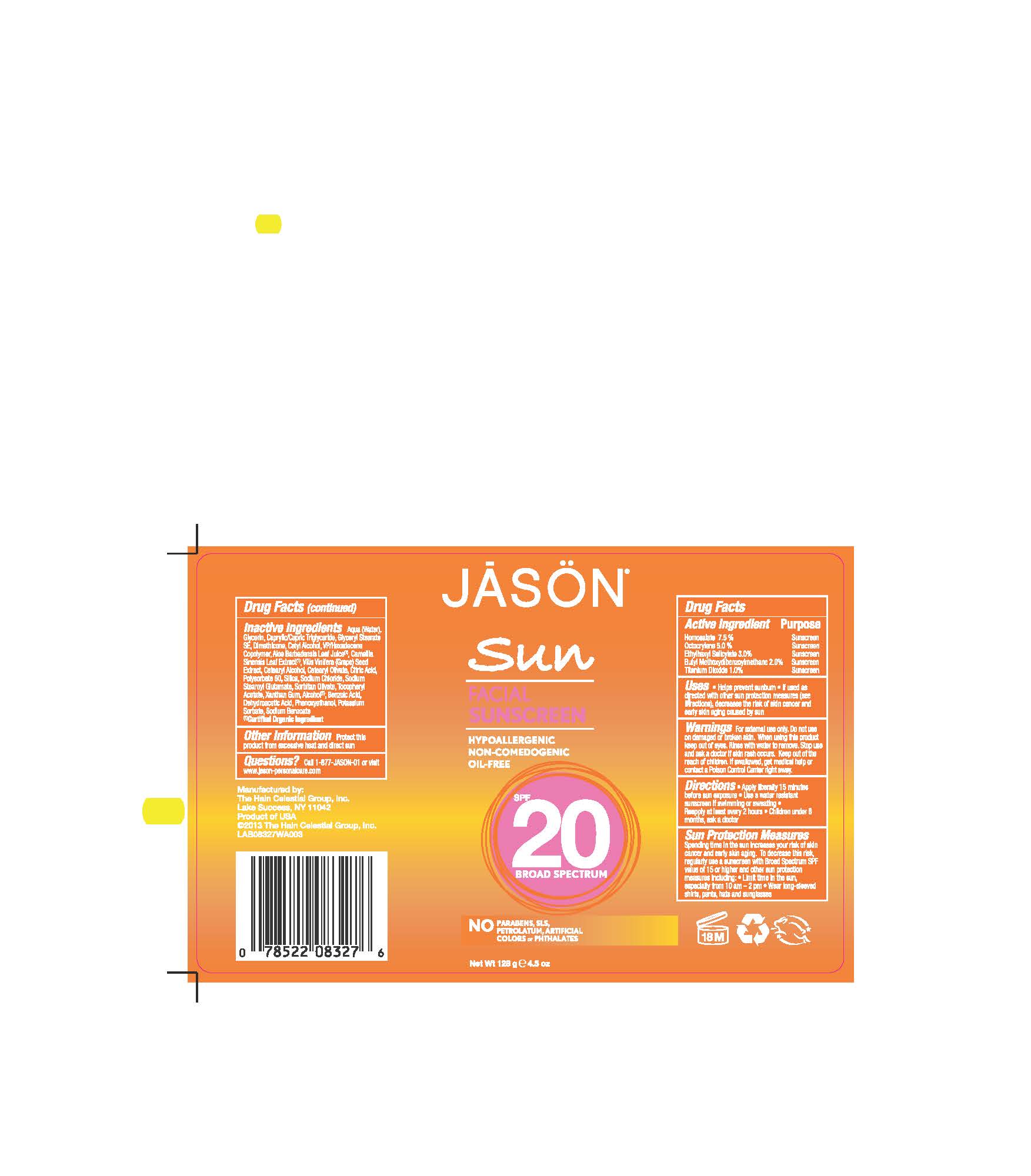 DRUG LABEL: Jason Sun Facial Sunscreen Broad Spectrum SPF20
NDC: 61995-0827 | Form: LOTION
Manufacturer: The Hain Celestial Group, Inc.
Category: otc | Type: HUMAN OTC DRUG LABEL
Date: 20150109

ACTIVE INGREDIENTS: HOMOSALATE 7.5 g/100 g; OCTISALATE 3 g/100 g; OCTOCRYLENE 5 g/100 g; AVOBENZONE 2 g/100 g; TITANIUM DIOXIDE 1 g/100 g
INACTIVE INGREDIENTS: CITRIC ACID MONOHYDRATE; GREEN TEA LEAF; ALOE VERA LEAF; GLYCERIN; WATER; VINYLPYRROLIDONE/HEXADECENE COPOLYMER; SODIUM STEAROYL GLUTAMATE; .ALPHA.-TOCOPHEROL ACETATE; GLYCERYL STEARATE SE; POTASSIUM SORBATE; CETYL ALCOHOL; DIMETHICONE; XANTHAN GUM; CETOSTEARYL ALCOHOL; DEHYDROACETIC ACID; POLYSORBATE 60; MEDIUM-CHAIN TRIGLYCERIDES; CETEARYL OLIVATE; SILICON DIOXIDE; SODIUM CHLORIDE; SORBITAN OLIVATE; SODIUM BENZOATE; ALCOHOL; PHENOXYETHANOL; VITIS VINIFERA SEED; BENZOIC ACID

Active Ingredient

Homosalate -7.5%

Octocrylene - 5.0%

Ethylhexyl Salicylate - 3.0%

Butyl Methoxydibenzoylmethane - 2.0%

Titanium Dioxide - 1.0%

DOSAGE AND ADMINISTRATION

Apply liberally 15 minutes before sun exposure. Use a water resistant sunscreen if swimming or sweating. Reapply at least every 2 hours.

PURPOSE

Sunscreen

WARNINGS

For external use only. Do not use on damaged or broken skin. When using this product keep out of eyes. Rinse with water to remove. Stop use and ask a doctor if skin rash occurs.

Keep out of reach of children. If swallowed get medical help or contact Poison Center right away.

INACTIVE INGREDIENT

Water, Glycerin, Glyceryl Stearate SE, Cetyl Alcohol, Dimethicone, Cetearyl Alcohol, VP/Hexadecene Copolymer, Caprylic/Capric Triglyceride, Aloe Barbadensis Leaf Juice(1), Camellia Sinensis Leaf Extract (1) Vitis Vinifera (Grape) Seed Extract, Cetearyl Olivate, Polysorbate 60, Benzoic Acid, Silica, Sodium Chloride, Sodium Stearoyl Glutamate, Sorbitan Olivate, Tocopheryl Acetate, Xanthan Gum, Alcohol (1), Citric Acid ,Dehydroacetic Acid, Phenoxyethanol, Potassium Sorbate, Sodium Benzoate.

(1) Certified Organic Ingredient

INDICATIONS AND USAGE

Helps prevents sunburns. If used as directed with other sun protection measures, decreases risk of skin cancer and early skin aging caused by sun exposure. Skin Protection Measures: Spending time in the sun increases your risk of skin cancer and early skin aging. To decrease risk, regularly use sunscreen with Broad Spectrum SPF 15 or higher and other protective measures including: limit time in sun, especially from10am to 2pm, and wear long sleeved shirts, pants, hats and sunglases.